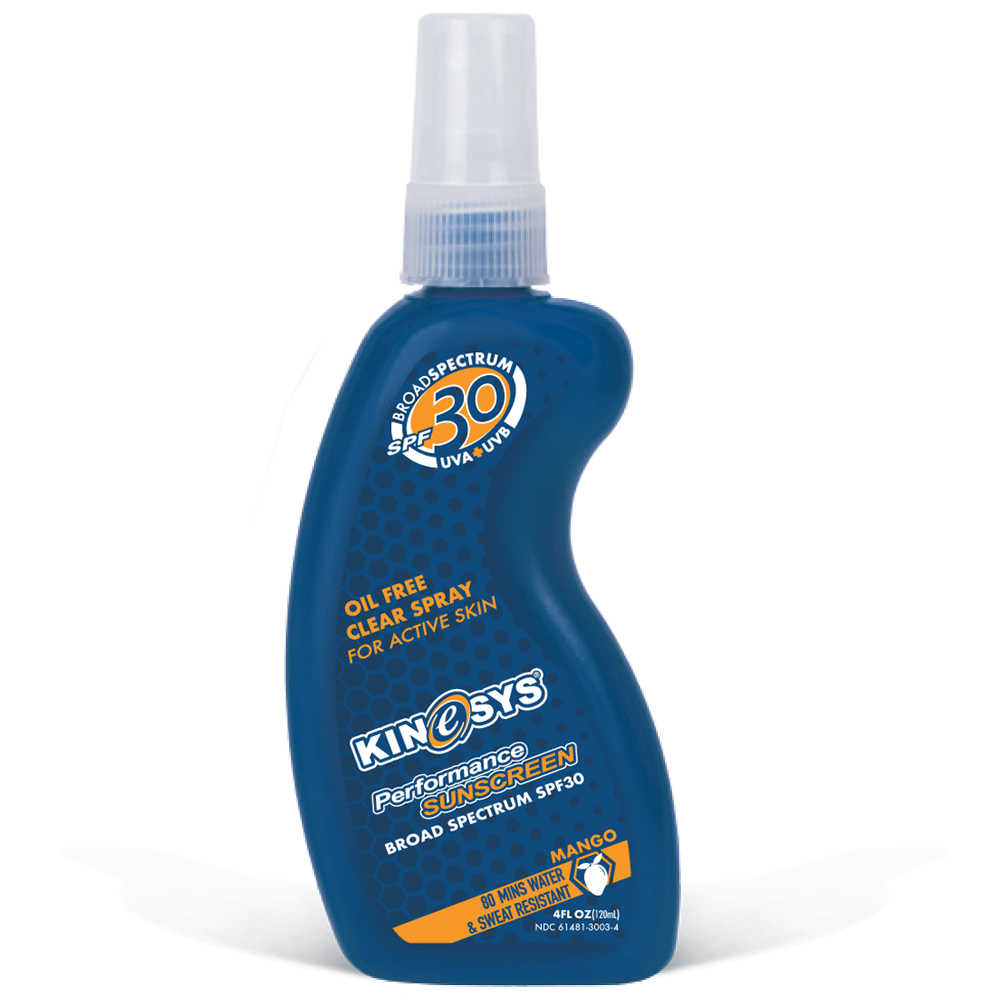 DRUG LABEL: Kinesys

NDC: 61481-3003 | Form: SPRAY
Manufacturer: Wilc Healthcare Inc
Category: otc | Type: HUMAN OTC DRUG LABEL
Date: 20251010

ACTIVE INGREDIENTS: OCTINOXATE 7.5 g/100 mL; OCTOCRYLENE 7.5 g/100 mL; OCTISALATE 5 g/100 mL; AVOBENZONE 2.5 g/100 mL
INACTIVE INGREDIENTS: CYCLOMETHICONE 5; ETHYLHEXYL PALMITATE; BUTYLOCTYL SALICYLATE; DIPHENYLSILOXY PHENYL TRIMETHICONE; VINYLPYRROLIDONE/HEXADECENE COPOLYMER; TOCOPHEROL; LEVOMENOL

Kinesys®Broad Spectrum SPF 30 Alcohol-Free Spray Sunscreen - Mango Scent

Active Ingredients

Octinoxate 7.5%
Octocrylene 7.5%
Octisalate 5.0%
Avobenzone 2.5%

Purpose

Sunscreen

Uses

- helps prevent sunburn
- if used as directed with other sun protection measures (see Directions), decreases the risk of skin cancer and early skin aging caused by the sun

Questions or Comments?

1-888-KINeSYS [546.3797]
www.kinesysactive.com

Warnings

For external use only

Do not use

- on damaged or broken skin

When using this product

- keep out of eyes. Rinse with water to remove.

Stop use and ask a doctor

- if rash occurs

Keep out of reach of children.

If product is swallowed, get medical help or contact a Poison Control Center right away.

Do not use

near flame or while smoking

Directions

- Hold container 4 to 6 inches from skin to apply.
- Spray generously and spread evenly by hand 15 minutes before sun exposure
- reapply:
  - after 80 minutes of swimming or sweating
  - immediately after towel drying
  - at least every 2 hours
- Do not spray directly onto the face. Spray into hands, and apply to the face.
- Do not apply in windy conditions.
- Use in well-ventilated area
- Sun Protection Measures.Spending time in the sun increases your risk of skin cancer and early skin aging. To decrease this risk, regularly use a sunscreen with a broad spectrum SPF of 15 or higher and other sun protection measures including:
  - limit time in the sun, especially from 10 a.m. – 2 p.m.
  - wear long-sleeve shirts, pants, hats, and sunglasses
  - children under 6 months:Ask a doctor

Inactive Ingredients

Bisabolol, Butyloctyl Salicylate, Cyclopentasiloxane, Diphenylsioxy Phenyl Trimethicone, Fragrance, Octyl Palmitate, Tocopherols, VP/ Hexadecene Copolymer.

Other Information

- protect this product from extreme temperatures. May stain or damage some fabrics and surfaces.

PRINCIPAL DISPLAY PANEL

120ML BOTTLE LABEL

BROAD SPECTRUM SPF 30 UVA + UVB

OIL FREE

CLEAR SPRAY

FOR ACTIVE SKIN

KINeSYS

Performance SUNSCREEN

BROAD SPECTRUM SPF30

MANGO

80 MINS WATER & SWEAT RESISTANT

4FL OZ(120ml)

NDC 61481-3003-4